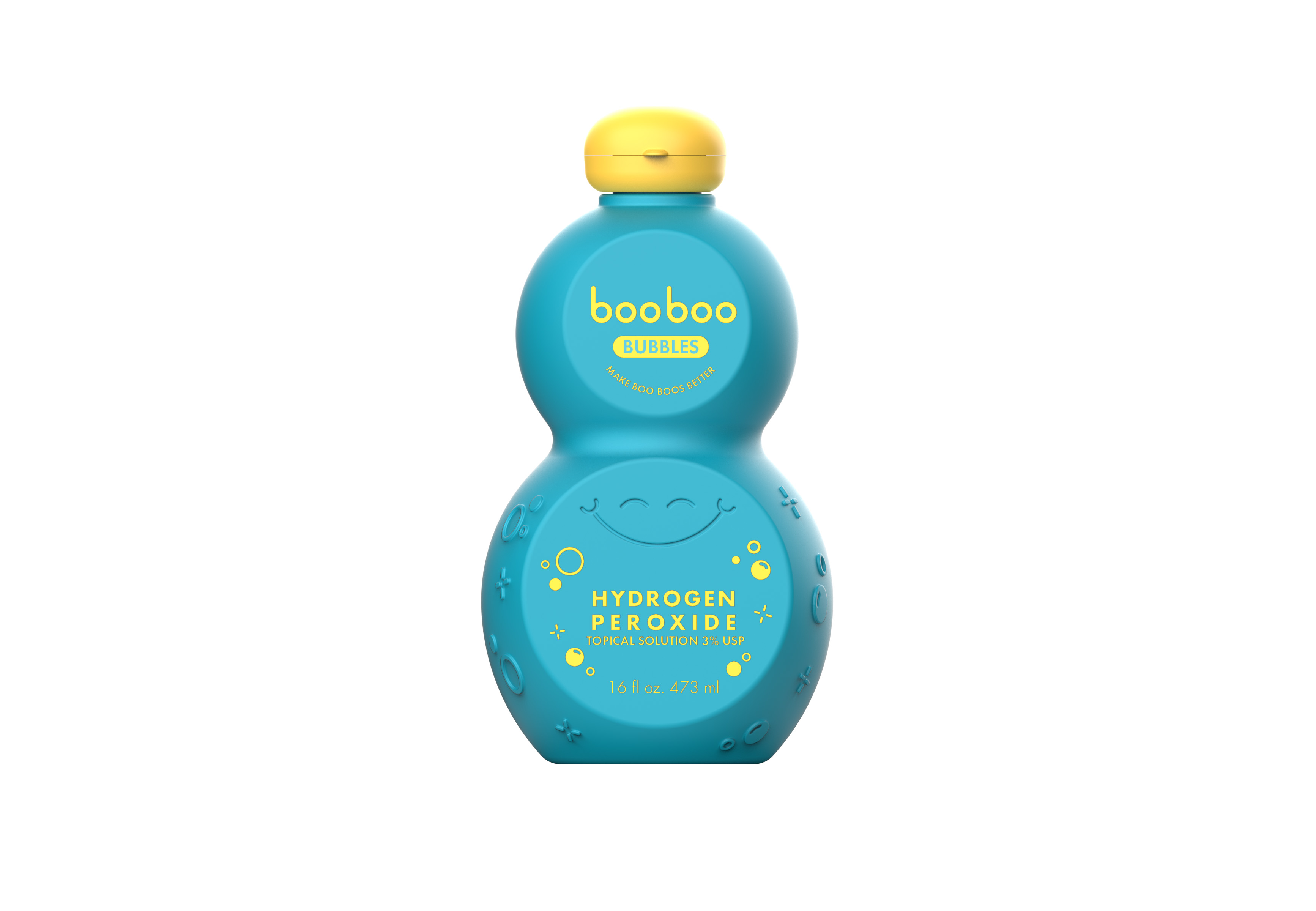 DRUG LABEL: Booboo Bubbles
NDC: 85324-001 | Form: SOLUTION
Manufacturer: 72 Seasons LLC
Category: otc | Type: HUMAN OTC DRUG LABEL
Date: 20250915

ACTIVE INGREDIENTS: HYDROGEN PEROXIDE 30 mg/1 mL
INACTIVE INGREDIENTS: WATER

Booboo Bubbles

Active Ingredient

Hydrogen Peroxide 3%

Purpose

Antiseptic

Indications

As an antiseptic to help prevent infection in minor cuts, scrapes, burns.

As an oral rinse for temporary use in cleaning minor wounds or irritation/inflammation to the mouth and gums resulting from minor dental procedures, orthodontic appliances or accidental injury.

Warnings

For external use except when used as an oral rinse

Do not use in the eyes

Do not apply over large areas of the body

Do not use longer than 1 weeks unless directed by a dentist or doctor

Ask a doctor before use if you have

Deep or puncture wounds

Animal bites

Serious burns

Sop use and consult a dentist or doctor if

condition persists or gets worse

sore mouth symptoms do not improve in 7 days

irritation, pain, redness or fever develop

Keep out of reach of children

In case of accidental ingestion, seek professional assistance or contact a Poison Control Cernter immediately.

Directions

For antiseptic use Clean the affected area. Apply a small amount on the area 1 to 3 times daily.

For oral rinse use Adults and children 2 years and older: Mix with an equal amount of water and swish around and over the affected area, then spit out. Use up to 4 times daily or as directed by a dentist or doctor. Children under 2 years of age: Consult a doctor.

Other Information

Keep tightly closed and at controlled room temperature 15o-30oC (59o-86oF). Do not shake.

Inactive Ingredient

Purified water